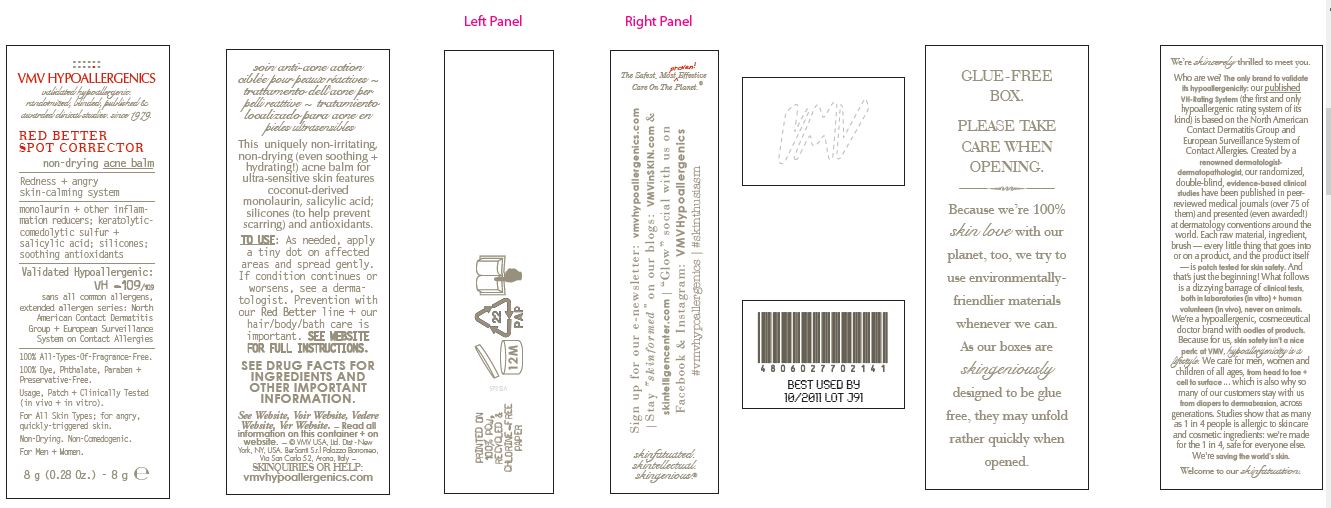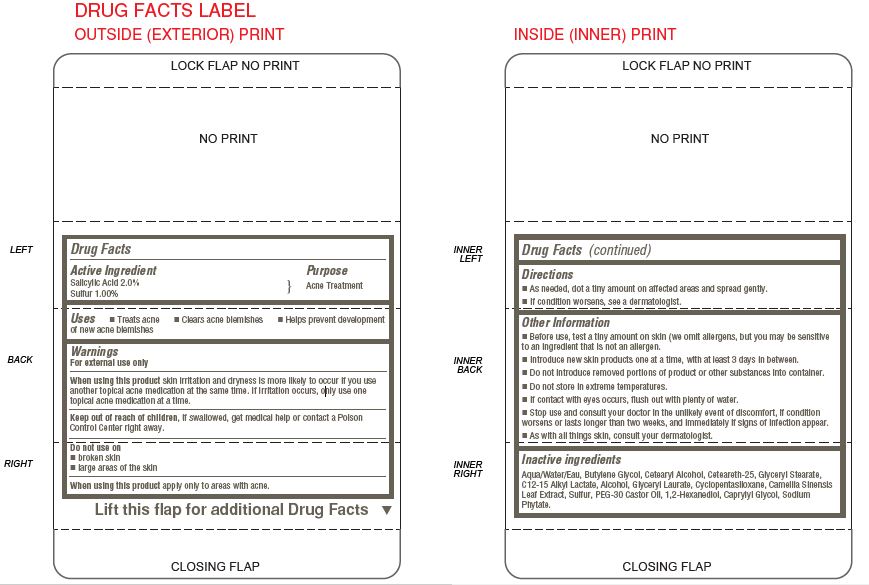 DRUG LABEL: RED BETTER SPOT CORRECTOR non-drying acne balm
NDC: 69774-944 | Form: CREAM
Manufacturer: SKIN SCIENCES LABORATORY INC.
Category: otc | Type: HUMAN OTC DRUG LABEL
Date: 20170529

ACTIVE INGREDIENTS: SULFUR 0.08 g/8 g; SALICYLIC ACID 0.16 g/8 g
INACTIVE INGREDIENTS: BUTYLENE GLYCOL; CETOSTEARYL ALCOHOL; CETEARETH-25; C12-15 ALKYL LACTATE; CYCLOMETHICONE 5; 1,2-HEXANEDIOL; CAPRYLYL GLYCOL; PHYTATE SODIUM; WATER; GLYCERYL MONOSTEARATE; GLYCERYL LAURATE; PEG-30 CASTOR OIL

VMV HYPOALLERGENICS RED BETTER SPOT CORRECTOR

Active Ingredient
Salicylic Acid 2.0%
Sulfur 1.00%

Purpose

Acne Treatment

INDICATIONS AND USAGE

Uses  Treats acne  Clears acne blemishes  Helps prevent development
of new acne blemishes

Warnings
For external use only
When using this product skin irritation and dryness is more likely to occur if you use
another topical acne medication at the same time. If irritation occurs, only use one
topical acne medication at a time.
Keep out of reach of children, if swallowed, get medical help or contact a Poison
Control Center right away.

Do not use on
 broken skin
 large areas of the skin
When using this product apply only to areas with acne.

Directions
 As needed, dot a tiny amount on affected areas and spread gently.
 If condition worsens, see a dermatologist.

Other Information
 Before use, test a tiny amount on skin (we omit allergens, but you may be sensitive
to an ingredient that is not an allergen.
 Introduce new skin products one at a time, with at least 3 days in between.
 Do not introduce removed portions of product or other substances into container.
 Do not store in extreme temperatures.
 If contact with eyes occurs, flush out with plenty of water.
 Stop use and consult your doctor in the unlikely event of discomfort, if condition
worsens or lasts longer than two weeks, and immediately if signs of infection appear.
 As with all things skin, consult your dermatologist.

Inactive Ingredients

Aqua/Water/Eau, Butylene Glycol, Cetearyl Alcohol, Ceteareth-25, Glyceryl Stearate,
C12-15 Alkyl Lactate, Alcohol, Glyceryl Laurate, Cyclopentasiloxane, Camellia Sinensis
Leaf Extract, Sulfur, PEG-30 Castor Oil, 1,2-Hexanediol, Caprylyl Glycol, Sodium
Phytate.

Keep out of reach of children, if swallowed, get medical help or contact a Poison
Control Center right away.

PACKAGE LABEL

VMV HYPOALLERGENICS
validated hypoallergenic.
randomized, blinded, published &
awarded clinical studies. since 1979

RED BETTER
SPOT CORRECTOR
non-drying acne balm

Redness + angry
skin-calming system

monolaurin + other inflammation reducers
keratolytic comedolytic sulfur +
salicylic acid; silicones;
soothing antioxidants

Validated
Hypoallergenic:
VH -109/109
sans all common allergens,
extended allergen series:
North American Contact Dermatitis
Group + European Surveillance
System on Contact Allergies

100% All-Types-Of-Fragrance-Free.

100% Dye, Phthalate, Paraben + Preservative-Free.

Usage, Patch + Clinically-Tested (in vitro + in vivo)

For All Skin Types; for angry, quickly-triggered skin.

Non-Drying. Non-Comedogenic.

For Men + Women.

8 g (0.28 Oz.) - 8g